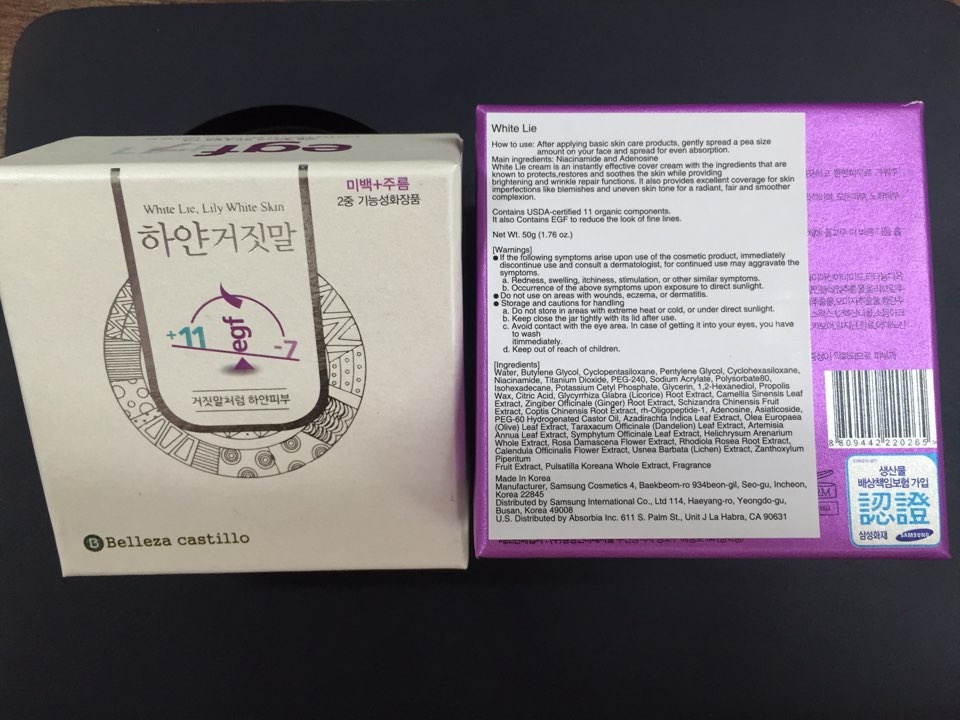 DRUG LABEL: White Lie
NDC: 70912-100 | Form: CREAM
Manufacturer: Samsung Cosmetics Co., LTD.
Category: otc | Type: HUMAN OTC DRUG LABEL
Date: 20160913

ACTIVE INGREDIENTS: ADENOSINE 0.02 g/50 g; NIACINAMIDE 1 g/50 g
INACTIVE INGREDIENTS: SODIUM ACRYLATE; USNEA BARBATA; ZANTHOXYLUM PIPERITUM FRUIT PULP; PULSATILLA KOREANA WHOLE; WATER; BUTYLENE GLYCOL; PENTYLENE GLYCOL; CYCLOMETHICONE 5; CYCLOMETHICONE 6; TITANIUM DIOXIDE; ISOHEXADECANE; POTASSIUM CETYL PHOSPHATE; GLYCERIN; 1,2-HEXANEDIOL; PROPOLIS WAX; ANHYDROUS CITRIC ACID; GLYCYRRHIZA GLABRA; CAMELLIA SINENSIS WHOLE; ZINGIBER OFFICINALE WHOLE; SCHISANDRA CHINENSIS FRUIT; COPTIS CHINENSIS ROOT; NEPIDERMIN; ASIATICOSIDE; PEG-60 CASTOR OIL; AZADIRACHTA INDICA LEAF; OLEA EUROPAEA LEAF; TARAXACUM OFFICINALE LEAF; ARTEMISIA ANNUA LEAF; SYMPHYTUM OFFICINALE WHOLE; HELICHRYSUM ARENARIUM WHOLE; ROSA DAMASCENA FLOWER OIL; RHODIOLA ROSEA ROOT; CALENDULA OFFICINALIS FLOWER; POLYSORBATE 80

Active Ingredient

Niacinamide 2.00%

Adenosine 0.04%

Purpose

Skin Protectant

Uses

- To protects, restores and soothes the skin
- To softening, smoothing, enhancing radiance and brightness skin

Directions

After applying basic skin care products, gently spread a pea size amount on your face and spread for even absorption

Warnings

For external use only

- Do not use on areas with wounds, eczema, or dermatitis.
- Stop using and ask a doctor if you have

a. Redness, swelling, itchiness, stimulation, or other similar symptoms.
b. Occurrence of the above symptoms upon exposure to direct sunlight.

- When using this product, keep out of eyes. Rinse with water to remove.

Keep out of reach of children. If product is swallowed, get medical help or contact a poison control center right away

Inactive Ingredients

Water, Butylene Glycol, Cyclopentasiloxane, Pentylene Glycol, Cyclohexasiloxane, Titanium Dioxide, PEG-240, Sodium Acrylate, Polysorbate80, Isohexadecane, Potassium Cetyl Phosphate, Glycerin, 1,2-Hexanediol, Propolis Wax, Citric Acid, Glycyrrhiza Glabra (Licorice) Root Extract, Camellia Sinensis Leaf Extract, Zingiber Officinale (Ginger) Root Extract, Schizandra Chinensis Fruit Extract, Coptis Chinensis Root Extract, rh-Oligopeptide-1, Asiaticoside, PEG-60 Hydrogenated Castor Oil, Azadirachta Indica Leaf Extract, Olea Europaea (Olive) Leaf Extract, Taraxacum Officinale (Dandelion) Leaf Extract, Artemisia Annua Leaf Extract, Symphytum Officinale Leaf Extract, Helichrysum Arenarium Whole Extract, Rosa Damascena Flower Extract, Rhodiola Rosea Root Extract, Calendula Officinalis Flower Extract, Usnea Barbata (Lichen) Extract, Zanthoxylum Piperitum Fruit Extract, Pulsatilla Koreana Whole Extract, Fragrance